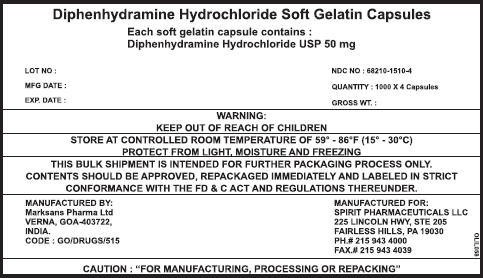 DRUG LABEL: DIPHENHYDRAMINE HYDROCHLORIDE
NDC: 68210-1510 | Form: CAPSULE, LIQUID FILLED
Manufacturer: SPIRIT PHARMACEUTICALS,LLC
Category: otc | Type: HUMAN OTC DRUG LABEL
Date: 20100726

ACTIVE INGREDIENTS: DIPHENHYDRAMINE HYDROCHLORIDE 50 mg/1 1
INACTIVE INGREDIENTS: POLYETHYLENE GLYCOL 400; PROPYLENE GLYCOL; GELATIN; SORBITOL; WATER; FD&C BLUE NO. 1

Diphenhydramine Hydrochloride Soft Gelatin Capsules

Drug Facts

Active ingredients (in each LiquiCap)

Diphenhydramine HCl 50 mg

Purpose

Nighttime Sleep aid

Uses

For relief occasional sleeplessness

Warnings

Do not use

- for children under 12 years of age
- with any other product containing Diphenhydramine, even one used on skin

Ask a doctor before use if you have

- Glaucoma
- trouble urinating due to enlarged postage gland
- a breathing problem such as emphysema or chronic bronchitis

Ask a doctor or pharmacist before use if you are taking sedatives or tranquilizers.

When using this product avoid alcoholic drinks

Stop use and ask doctor if

- sleeplessness persists continuously for more than 2 weeks. Insomnia may be a symptom of serious underlying medical illness.

PREGNANCY OR BREAST FEEDING

If pregnant or breast-feeding, ask a health professional before use

Keep out of reach of children.

In case of overdose,get medical help or contact a poison control center right away.

Direction

adults and children 12 years of age and older -1 softgel (50mg) at bedtime if needed; or as directed by doctor

Inactive ingredients

PEG – 400, Propylene Glycol USP , Gelatin , Sorbitol, FD & C Blue No.1 IH, Purified water

PRINCIPAL DISPLAY PANEL - 50 mg Shipper Label

Diphenhydramine Hydrochloride Soft Gelatin Capsules

Each soft gelatin capsule contains:
Diphenhydramine Hydrochloride USP 50 mg

LOT NO :

MFG DATE :

EXP. DATE :

NDC NO : 68210-1510-4

QUANTITY : 1000 × 4 Capsules

GROSS WT. :

WARNING:
KEEP OUT OF REACH OF CHILDREN

STORE AT CONTROLLED ROOM TEMPERATURE OF 59° - 86°F (15° - 30°C)
PROTECT FROM LIGHT, MOISTURE AND FREEZING

THIS BULK SHIPMENT IS INTENDED FOR FURTHER PACKAGING PROCESS ONLY.
CONTENTS SHOULD BE APPROVED, REPACKAGED IMMEDIATELY AND LABELED IN STRICT
CONFORMANCE WITH THE FD & C ACT AND REGULATIONS THEREUNDER.

MANUFACTURED BY:
Marksans Pharma Ltd
VERNA, GOA-403722,
INDIA.
CODE : GO/DRUGS/515

MANUFACTURED FOR:
SPIRIT PHARMACEUTICALS LLC
225 LINCOLN HWY, STE 205
FAIRLESS HILLS, PA 19030
PH.# 215 943 4000
FAX.# 215 943 4039

CAUTION : "FOR MANUFACTURING, PROCESSING OR REPACKING"

OLIL058